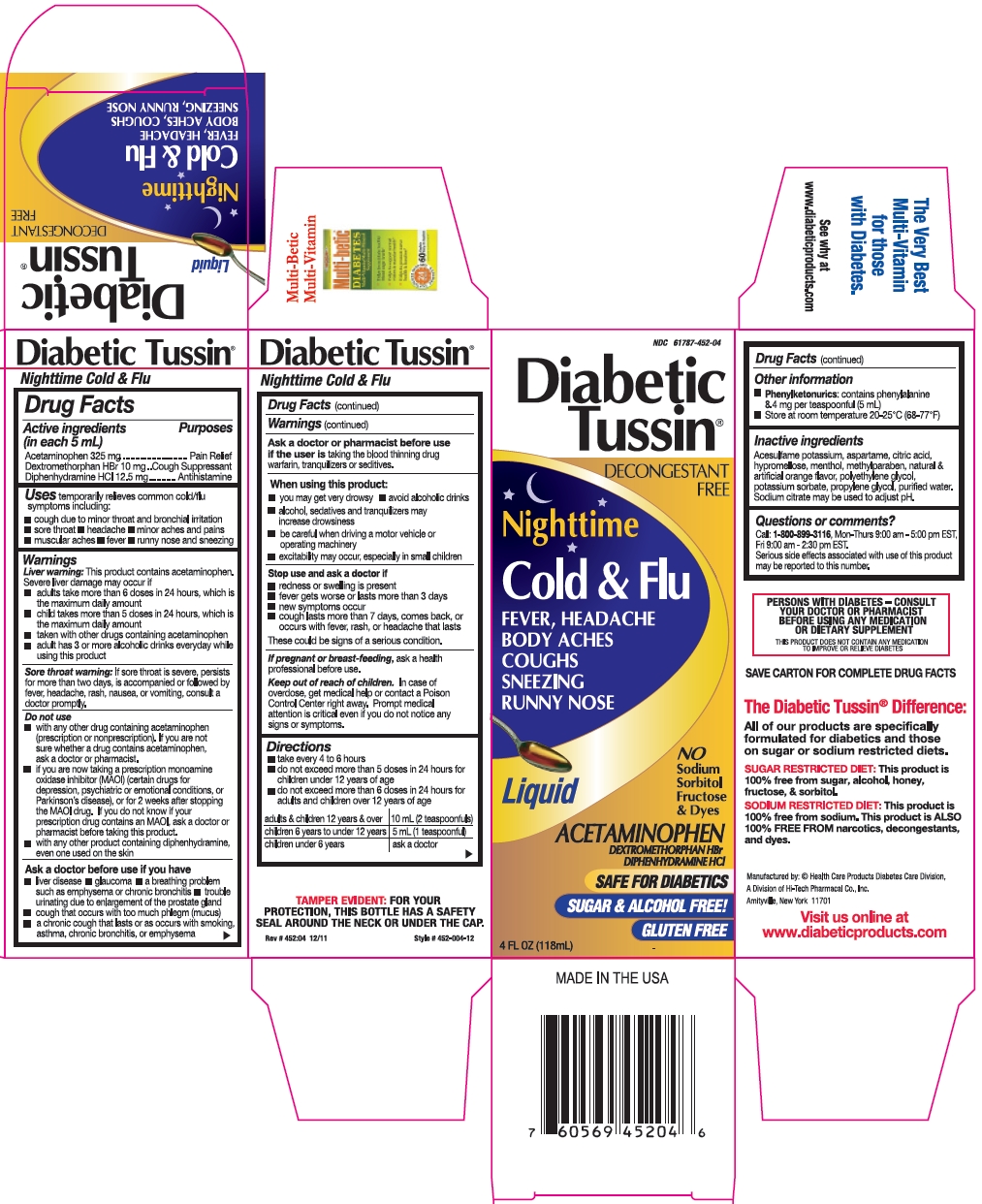 DRUG LABEL: Diabetic Tussin Nighttime Cold and Flu
NDC: 61787-452 | Form: LIQUID
Manufacturer: Health Care Products
Category: otc | Type: HUMAN OTC DRUG LABEL
Date: 20191217

ACTIVE INGREDIENTS: ACETAMINOPHEN 325 mg/5 mL; DEXTROMETHORPHAN HYDROBROMIDE 10 mg/5 mL; DIPHENHYDRAMINE HYDROCHLORIDE 12.5 mg/5 mL
INACTIVE INGREDIENTS: WATER; ASPARTAME; ACESULFAME POTASSIUM; HYPROMELLOSE 2910 (4000 MPA.S); POLYETHYLENE GLYCOL 400; POTASSIUM SORBATE; ANHYDROUS CITRIC ACID; PROPYLENE GLYCOL; METHYLPARABEN; MENTHOL, UNSPECIFIED FORM; TRISODIUM CITRATE DIHYDRATE

Drug Facts

Active ingredients (in each 5 mL)

Acetaminophen 325 mg

Dextromethorphan HBr 10 mg

Diphenhydramine HCl 12.5 mg

Purposes

Pain Relief

Cough Suppressant

Antihistamine

Uses

temporarily relieves common cold/flu symptoms including:

- cough due to minor throat and bronchial irritation
- sore throat
- headache
- minor aches and pains
- muscular aches
- fever
- runny nose and sneezing

Warnings

Liver warning: This product contains acetaminophen. Severe liver damage may occur if

- adults take more than 6 doses in 24 hours, which is the maximum daily amount
- child takes more than 5 doses in 24 hours, which is the maximum daily amount
- taken with other drugs containing acetaminophen
- adult has 3 or more alcoholic drinks everyday while using this product

Sore throat warning: If sore throat is severe, persists for more than two days, is accompanied or followed by fever, headache, rash, nausea, or vomiting, consult a doctor promptly.

Do not use

- with any other drug containing acetaminophen (prescription or nonprescription). If you are not sure whether a drug contains acetaminophen, ask a doctor or pharmacist.
- if you are now taking a prescription monoamine oxidase inhibitor (MAOI) (certain drugs for depression, psychiatric or emotional conditions, or Parkinson's disease), or for 2 weeks after stopping the MAOI drug. If you do not know if your prescription drug contains an MAOI, ask a doctor or pharmacist before taking this product.
- with any other product containing diphenhydramine, even one used on the skin

Ask a doctor before use if you have

- liver disease
- glaucoma
- a breathing problem such as emphysema or chronic bronchitis
- trouble urinating due to enlargement of the prostate gland
- cough that occurs with too much phlegm (mucus)
- a chronic cough that lasts or as occurs with smoking, asthma, chronic bronchitis, or emphysema

Ask a doctor or pharmacist before use

if the user is taking the blood thinning drug warfarin, tranquilizers or sedatives.

When using this product:

- you may get very drowsy
- avoid alcoholic drinks
- alcohol, sedatives and tranquilizers may increase drowsiness
- be careful when driving a motor vehicle or operating machinery
- excitability may occur, especially in small children

Stop use and ask a doctor if

- redness or swelling is present
- fever gets worse or lasts more than 3 days
- new symptoms occur
- cough lasts more than 7 days, comes back, or occurs with fever, rash, or headache that lasts

These could be signs of a serious condition.

If pregnant or breast-feeding,

ask a health professional before use.

Keep out of reach of children.

In case of overdose, get medical help or contact a Poison Control Center right away. Prompt medical attention is critical even if you do not notice any signs or symptoms.

Directions

- take every 4 to 6 hours
- do not exceed more than 5 doses in 24 hours for children under 12 years of age
- do not exceed more than 6 doses in 24 hours for adults and children over 12 years of age

adults & children 12 years & over | 10 mL (2 teaspoonfuls)
children 6 years to under 12 years | 5 mL (1 teaspoonful)
children under 6 years | ask a doctor

Other information

- Phenylketonurics: contains phenylalanine 8.4 mg per teaspoonful (5 mL)
- Store at room temperature 20-25°C (68-77°F)

Inactive ingredients

Acesulfame potassium, aspartame, citric acid, hypromellose, menthol, methylparaben, natural & artificial orange flavor, polyethylene glycol, potassium sorbate, propylene glycol, purified water. Sodium citrate may be used to adjust pH.

Questions or comments?

Call: 1-800-899-3116, Mon-Thurs 9:00 am - 5:00 pm EST, Fri 9:00 am - 2:30 pm EST.

Serious side effects associated with use of this product may be reported to this number.

Rev. 452:04 12/11

Package/Label Principal Display Panel

NDC 61787-452-04

Diabetic Tussin®

DECONGESTANT FREE

Nighttime

Cold & Flu

FEVER, HEADACHE

BODY ACHES

COUGHS

SNEEZING

RUNNY NOSE

Liquid

NO

Sodium

Sorbitol

Fructose

& Dyes

ACETAMINOPHEN

DEXTROMETHORPHAN HBr

DIPHENHYDRAMINE HCl

SAFE FOR DIABETICS

SUGAR & ALCOHOL FREE!

GLUTEN FREE

4 FL OZ (118 mL)